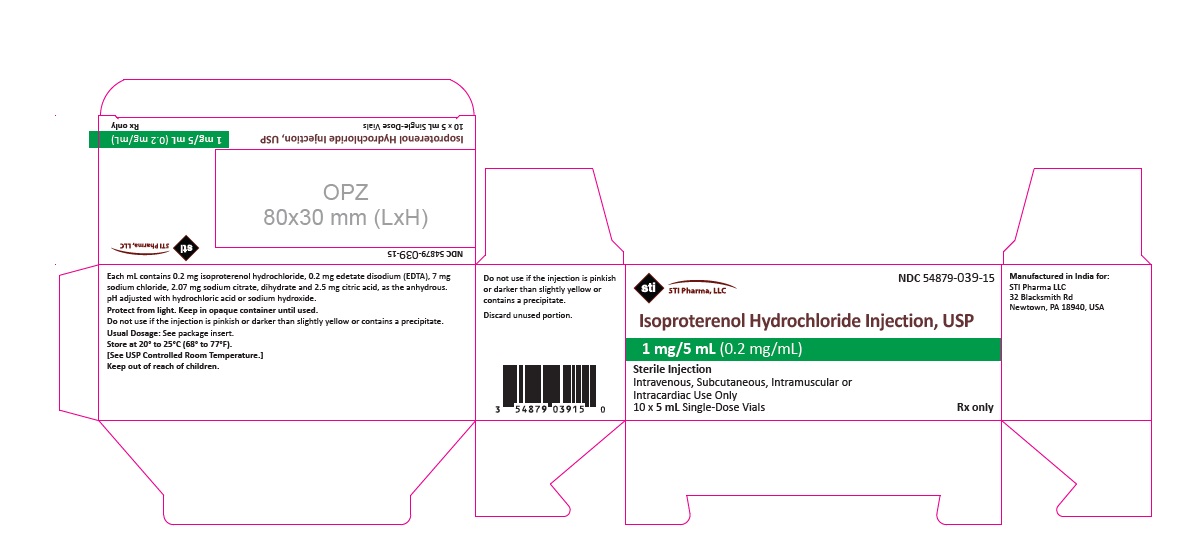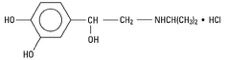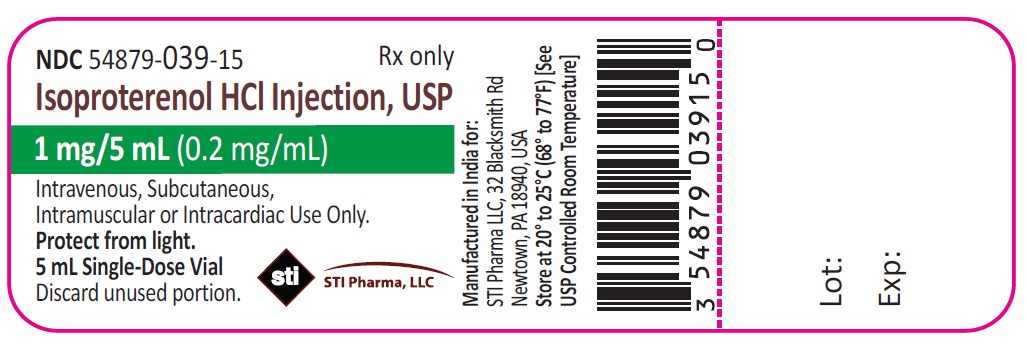 DRUG LABEL: Isoproterenol Hydrochloride
NDC: 54879-039 | Form: INJECTION, SOLUTION
Manufacturer: STI Pharma LLC
Category: prescription | Type: HUMAN PRESCRIPTION DRUG LABEL
Date: 20221003

ACTIVE INGREDIENTS: ISOPROTERENOL HYDROCHLORIDE 1 mg/5 mL
INACTIVE INGREDIENTS: ANHYDROUS CITRIC ACID; EDETATE DISODIUM; HYDROCHLORIC ACID; SODIUM CHLORIDE; SODIUM HYDROXIDE; SODIUM CITRATE; WATER

Isoproterenol Hydrochloride Injection, USP
Sterile Injection
Rx only

DESCRIPTION

Isoproterenol hydrochloride is 3,4-Dihydroxy-α-[(isopropylamino)methyl] benzyl alcohol hydrochloride, a synthetic sympathomimetic amine that is structurally related to epinephrine but acts almost exclusively on beta receptors. The molecular formula is C11H17NO3 • HCl. It has a molecular weight of 247.72 and the following structural formula:

Isoproterenol hydrochloride is a racemic compound.

Each milliliter of the sterile solution contains:

Isoproterenol hydrochloride injection, USP | 0.2 mg
Edetate Disodium (EDTA) | 0.2 mg
Sodium Chloride | 7.0 mg
Sodium Citrate, Dihydrate | 2.07 mg
Citric Acid, Anhydrous | 2.5 mg
Water for Injection | 1.0 mL

The pH is adjusted between 2.5 and 4.5 with hydrochloric acid or sodium hydroxide.

The sterile solution is nonpyrogenic and can be administered by the intravenous, intramuscular, subcutaneous or intracardiac routes.

CLINICAL PHARMACOLOGY

Isoproterenol is a potent nonselective beta-adrenergic agonist with very low affinity for alpha-adrenergic receptors. Intravenous infusion of isoproterenol in man lowers peripheral vascular resistance, primarily in skeletal muscle but also in renal and mesenteric vascular beds. Diastolic pressure falls. Renal blood flow is decreased in normotensive subjects but is increased markedly in shock. Systolic blood pressure may remain unchanged or rise, although mean arterial pressure typically falls. Cardiac output is increased because of the positive inotropic and chronotropic effects of the drug in the face of diminished peripheral vascular resistance. The cardiac effects of isoproterenol may lead to palpitations, sinus tachycardia, and more serious arrhythmias; large doses of isoproterenol may cause myocardial necrosis in animals.

Isoproterenol relaxes almost all varieties of smooth muscle when the tone is high, but this action is most pronounced on bronchial and gastrointestinal smooth muscle. It prevents or relieves bronchoconstriction, but tolerance to this effect develops with overuse of the drug.

In man, isoproterenol causes less hyperglycemia than does epinephrine. Isoproterenol and epinephrine are equally effective in stimulating the release of free fatty acids and energy production.

Absorption, Fate, and Excretion Isoproterenol is metabolized primarily in the liver and other tissues by COMT. Isoproterenol is a relatively poor substrate for MAO and is not taken up by sympathetic neurons to the same extent as are epinephrine and norepinephrine. The duration of action of isoproterenol may therefore be longer than that of epinephrine, but is still brief.

INDICATIONS AND USAGE

Isoproterenol hydrochloride injection is indicated:

- For mild or transient episodes of heart block that do not require electric shock or pacemaker therapy.
- For serious episodes of heart block and Adams-Stokes attacks (except when caused by ventricular tachycardia or fibrillation). (see CONTRAINDICATIONS)
- For use in cardiac arrest until electric shock or pacemaker therapy, the treatments of choice, is available. (see CONTRAINDICATIONS)
- For bronchospasm occurring during anesthesia.
- As an adjunct to fluid and electrolyte replacement therapy and the use of other drugs and procedures in the treatment of hypovolemic and septic shock, low cardiac output (hypoperfusion) states, congestive heart failure, and cardiogenic shock. (see WARNINGS)

CONTRAINDICATIONS

Use of isoproterenol hydrochloride injection is contraindicated in patients with tachyarrhythmias; tachycardia or heart block caused by digitalis intoxication; ventricular arrhythmias which require inotropic therapy; and angina pectoris.

WARNINGS

Isoproterenol hydrochloride injection, by increasing myocardial oxygen requirements while decreasing effective coronary perfusion, may have a deleterious effect on the injured or failing heart. Most experts discourage its use as the initial agent in treating cardiogenic shock following myocardial infarction. However, when a low arterial pressure has been elevated by other means, isoproterenol hydrochloride injection may produce beneficial hemodynamic and metabolic effects.

In a few patients, presumably with organic disease of the AV node and its branches, isoproterenol hydrochloride injection has paradoxically been reported to worsen heart block or to precipitate Adams-Stokes attacks during normal sinus rhythm or transient heart block.

PRECAUTIONS

General

Isoproterenol hydrochloride injection should generally be started at the lowest recommended dose. This may be gradually increased if necessary while carefully monitoring the patient. Doses sufficient to increase the heart rate to more than 130 beats per minute may increase the likelihood of inducing ventricular arrhythmias. Such increases in heart rate will also tend to increase cardiac work and oxygen requirements which may adversely affect the failing heart or the heart with a significant degree of arteriosclerosis.

Adequate filling of the intravascular compartment by suitable volume expanders is of primary importance in most cases of shock and should precede the administration of vasoactive drugs. In patients with normal cardiac function, determination of central venous pressure is a reliable guide during volume replacement. If evidence of hypoperfusion persists after adequate volume replacement, isoproterenol hydrochloride injection may be given.

In addition to the routine monitoring of systemic blood pressure, heart rate, urine flow, and the electrocardiograph, monitor the response to therapy by frequent determination of the central venous pressure and blood gases. Closely observe patients in shock during isoproterenol hydrochloride injection administration. If the heart rate exceeds 110 beats per minute, it may be advisable to decrease the infusion rate or temporarily discontinue the infusion. Determinations of cardiac output and circulation time may also be helpful. Take appropriate measures to ensure adequate ventilation. Pay attention to acid-base balance and to the correction of electrolyte disturbances.

Drug Interactions

Isoproterenol hydrochloride injection and epinephrine should not be administered simultaneously because both drugs are direct cardiac stimulants and their combined effects may induce serious arrhythmias. The drugs may, however, be administered alternately provided a proper interval has elapsed between doses.

Avoid isoproterenol hydrochloride injection when potent inhalational anesthetics such as halothane are employed because of potential to sensitize the myocardium to effects of sympathomimetic amines.

Carcinogenesis, Mutagenesis, Impairment of Fertility

Long-term studies in animals to evaluate the carcinogenic potential of isoproterenol hydrochloride have not been done. Mutagenic potential and effect on fertility have not been determined. There is no evidence from human experience that isoproterenol hydrochloride injection may be carcinogenic or mutagenic or that it impairs fertility.

Pregnancy

Animal reproduction studies have not been conducted with isoproterenol hydrochloride. It is also not known whether isoproterenol hydrochloride can cause fetal harm when administered to a pregnant woman or can affect reproduction capacity. Isoproterenol hydrochloride should be given to a pregnant woman only if clearly needed.

Nursing Mothers

It is not known whether this drug is excreted in human milk. Because many drugs are excreted in human milk, caution should be exercised when isoproterenol hydrochloride injection is administered to a nursing woman.

Pediatric Use

Safety and efficacy of isoproterenol in pediatric patients have not been established.

Intravenous infusions of isoproterenol in refractory asthmatic children at rates of 0.05-2.7 mcg/kg/min have caused clinical deterioration, myocardial necrosis, congestive heart failure and death. The risks of cardiac toxicity appear to be increased by some factors [acidosis, hypoxemia, coadministration of corticosteroids, coadministration of methylxanthines (theophylline, theobromine) or aminophylline] that are especially likely to be present in these patients. If I.V. isoproterenol is used in children with refractoryasthma, patient monitoring must include continuous assessment of vital signs, frequent electrocardiography, and daily measurements of cardiac enzymes, including CPK-MB.

Geriatric Use

Clinical studies of isoproterenol hydrochloride injection did not include sufficient numbers of subjects aged 65 and over to determine whether they respond differently from younger subjects in clinical circumstances. There are, however, some data that suggest that elderly healthy or hypertensive patients are less responsive to beta-adrenergic stimulation than are younger subjects. In general, dose selection for elderly patients should usually start at the low end of the dosing range, reflecting the greater frequency of decreased hepatic, renal or cardiac function and of concomitant diseases or other drug therapy.

ADVERSE REACTIONS

The following reactions to isoproterenol hydrochloride injection have been reported:

CNS: Nervousness, headache, dizziness, nausea, visual blurring.

Cardiovascular: Tachycardia, palpitations, angina, Adams-Stokes attacks, pulmonary edema, hypertension, hypotension, ventricular arrhythmias, tachyarrhythmias.

In a few patients, presumably with organic disease of the AV node and its branches, isoproterenol hydrochloride injection has been reported to precipitate Adams-Stokes seizures during normal sinus rhythm or transient heart block.

Respiratory: Dyspnea.

Other: Flushing of the skin, sweating, mild tremors, weakness, pallor.

To report SUSPECTED ADVERSE REACTIONS, contact STI Pharma LLC at 1-888-301-9680 or FDA at 1-800-FDA-1088 or www.fda.gov/medwatch.

OVERDOSAGE

The acute toxicity of isoproterenol hydrochloride in animals is much less than that of epinephrine.

Excessive doses in animals or man can cause a striking drop in blood pressure, and repeated large doses in animals may result in cardiac enlargement and focal myocarditis.

In case of accidental overdosage as evidenced mainly by tachycardia or other arrhythmias, palpitations, angina, hypotension, or hypertension, reduce rate of administration or discontinue isoproterenol hydrochloride injection until patient’s condition stabilizes. Blood pressure, pulse, respiration, and ECG should be monitored.

It is not known whether isoproterenol hydrochloride is dialyzable.

The oral LD50 of isoproterenol hydrochloride in mice is 3,850 mg/kg ± 1,190 mg/kg of pure drug in solution.

DOSAGE AND ADMINISTRATION

Start isoproterenol hydrochloride injection at the lowest recommended dose and increase the rate of administration gradually if necessary while carefully monitoring the patient. The usual route of administration is by intravenous infusion or bolus intravenous injection. In dire emergencies, the drug may be administered by intracardiac injection. If time is not of the utmost importance, initial therapy by intramuscular or subcutaneous injection is preferred.

Recommended dosage for adults with heart block, Adams-Stokes attacks, and cardiac arrest:
Route of; Administration | Preparation of Dilution | Initial Dose | Subsequent Dose; Range [Subsequent dosage and method of administration depend on the ventricular rate and the rapidity with which the cardiac pacemaker can take over when the drug is gradually withdrawn.]
Bolus; intravenous; injection | Dilute 1 mL (0.2 mg) in 9 mL of Sodium Chloride Injection, USP, or 5% Dextrose Injection, USP | 0.02 mg to 0.06 mg; (1 mL to 3 mL of; diluted solution) | 0.01 mg to 0.2 mg; (0.5 mL to 10 mL; of diluted solution)
Intravenous; infusion | Dilute 10 mL (2 mg) in 500 mL; of 5% Dextrose Injection, USP | 5 mcg/min. (1.25 mL; of diluted solution; per minute)
Intramuscular | Use Solution undiluted | 0.2 mg (1 mL) | 0.02 mg to 1 mg; (0.1 mL to 5 mL)
Subcutaneous | Use Solution undiluted | 0.2 mg (1 mL) | 0.15 mg to 0.2 mg; (0.75 mL to 1 mL)
Intracardiac | Use Solution undiluted | 0.02 mg (0.1 mL)

There are no well-controlled studies in children to establish appropriate dosing; however, the American Heart Association recommends an initial infusion rate of 0.1 mcg/kg/min, with the usual range being 0.1 mcg/kg/min to 1 mcg/kg/min.

Recommended dosage for adults with shock and hypoperfusion states:
Route of Administration | Preparation of Dilution [Concentrations up to 10 times greater have been used when limitation of volume is essential.] | Infusion Rate [Rates over 30 mcg per minute have been used in advanced stages of shock. The rate of infusion should be adjusted on the basis of heart rate, central venous pressure, systemic blood pressure, and urine flow. If the heart rate exceeds 110 beats per minute, it may be advisable to decrease or temporarily discontinue the infusion.]
Intravenous infusion | Dilute 5 mL (1 mg) in 500 mL; of 5% Dextrose Injection, USP | 0.5 mcg to 5 mcg per minute; (0.25 mL to 2.5 mL of diluted solution)

Recommended dosage for adults with bronchospasm occurring during anesthesia:
Route of; Administration | Preparation of Dilution | Initial Dose | Subsequent Dose
Bolus intravenous; injection | Dilute 1 mL (0.2 mg) in; 9 mL of Sodium Chloride Injection, USP, or 5% Dextrose Injection, USP | 0.01 mg to 0.02 mg; (0.5 mL to 1 mL of; diluted solution) | The initial dose may; be repeated when; necessary

Parenteral drug products should be inspected visually for particulate matter and discoloration prior to administration, whenever solution and container permit. Such solution should not be used.

Discard unused portion.

HOW SUPPLIED

NDC Number | Container | Concentration | Fill | Quantity
54879-039-15 | Single-Dose Vial | 1 mg/5 mL (0.2 mg/mL) | 5 mL | 10 × 5 mL Single Dose Vials

Protect from light. Keep in opaque container until used.

Store at 20º to 25ºC (68º to 77ºF). [See USP Controlled Room Temperature.]

Do not use if the injection is pinkish or darker than slightly yellow or contains a precipitate.

Manufactured in India for:
STI Pharma LLC
32 Blacksmith Rd
Newtown, PA 18940, USA

Revised: 05/2021

PACKAGE LABEL

NDC 54879-039-15
Rx only

Isoproterenol HCl Injection, USP

1 mg/5 mL (0.2 mg/mL)

Intravenous, Subcutaneous,
Intramuscular or Intracardiac Use Only.

Protect from light.
5 mL Single-Dose Vial

Discard unused portion.

STI Pharma, LLC

NDC 54879-039-15

STI Pharma, LLC

Isoproterenol Hydrochloride Injection, USP

1 mg/5 mL (0.2 mg/mL)

Sterile Injection

Intravenous, Subcutaneous, Intramuscular or
Intracardiac Use Only
10 x 5 mL Single-Dose Vials

Rx only